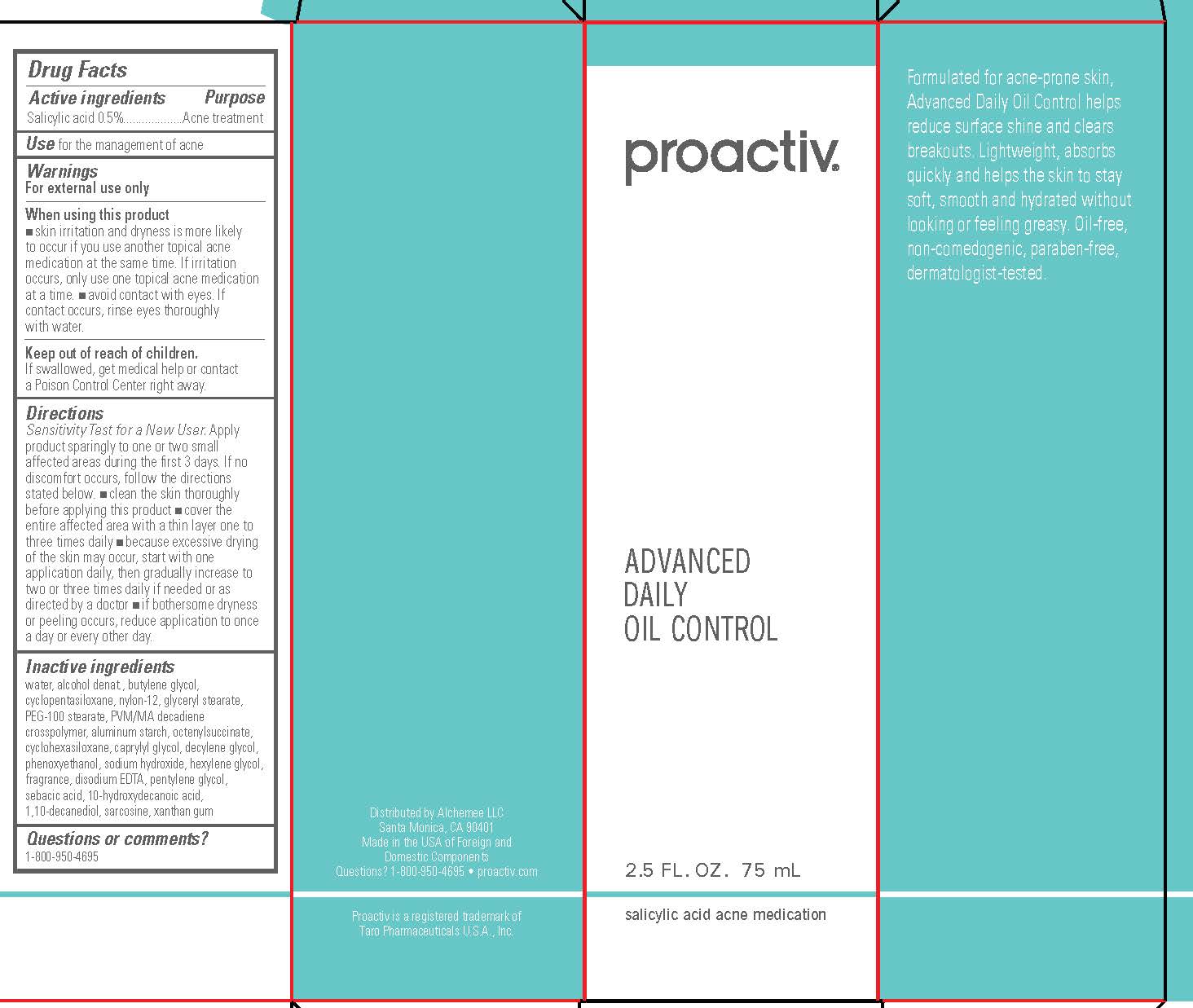 DRUG LABEL: Proactiv Advanced Daily Oil Control
NDC: 11410-055 | Form: LOTION
Manufacturer: Alchemee, LLC
Category: otc | Type: HUMAN OTC DRUG LABEL
Date: 20260107

ACTIVE INGREDIENTS: SALICYLIC ACID 0.5 mg/100 mL
INACTIVE INGREDIENTS: NYLON-12; ALUMINUM STARCH OCTENYLSUCCINATE; CYCLOMETHICONE 6; WATER; BUTYLENE GLYCOL; CYCLOMETHICONE 5; GLYCERYL MONOSTEARATE; PEG-100 STEARATE; DECYLENE GLYCOL; CAPRYLYL GLYCOL; HEXYLENE GLYCOL; PENTYLENE GLYCOL; 10-HYDROXYDECANOIC ACID; SEBACIC ACID; 1,10-DECANEDIOL; SARCOSINE; XANTHAN GUM; SODIUM HYDROXIDE; EDETATE DISODIUM; PHENOXYETHANOL; ALCOHOL

Proactiv®Advanced Daily Oil Control

Active Ingredient

Salicylic Acid 0.5%

Purpose

Acne treatment

Use

for the management of acne

Warnings

For external use only

When using this product

- skin irritation and dryness is more likely to occur if you use another topical acne medication at the same time. If irritation occurs, only use one topical acne medication at a time.
- avoid contact with eyes. If contact occurs, rinse eyes thoroughly with water.

Keep out of reach of children.If swallowed, get medical help or contact a Poison Control Center right away.

Directions

- Sensitivity Test for a New User. Apply product sparingly to one or two small affected areas during the first 3 days. If no discomfort occurs, follow the directions stated below.
- clean the skin thoroughly before applying this product.
- cover the entire affected area with a thin layer one to three times daily.
- because excessive drying of the skin may occur, start with one application daily, then gradually increase to two or three times daily if needed or as directed by a doctor.
- if bothersome dryness or peeling occurs, reduce application to once a day or every other day.

Inactive Ingredients

water, alcohol denat., butylene glycol, cyclopentasiloxane, nylon-12, glyceryl stearate, PEG-100 stearate, PVM/MA decadiene crosspolymer, aluminum starch octenylsuccinate, cyclohexasiloxane, caprylyl glycol, decylene glycol, phenoxyethanol, sodium hydroxide, hexylene glycol, fragrance, disodium EDTA, pentylene glycol, sebacic acid, 10-hydroxydecanoic acid, 1,10-decanediol, sarcosine, xanthan gum

Questions or comments?
1-800-950-4695

Distributed by Alchemee LLC
Santa Monica, CA 90401
Made in the USA of Foreign and
Domestic Components
Questions? 1-800-950-4695 • proactiv.com
Proactiv is a registered trademark of
Taro Pharmaceuticals U.S.A., Inc.

PRINCIPAL DISPLAY PANEL - 75 mL Carton

proactiv®

ADVANCED
DAILY
OIL CONTROL

2.5 FL. OZ. 75 mL

salicylic acid acne medication